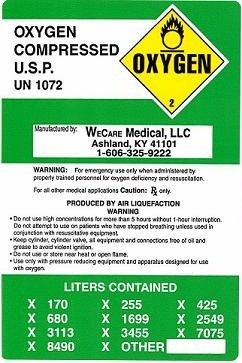 DRUG LABEL: Oxygen
NDC: 50198-2826 | Form: GAS
Manufacturer: WeCare Medical LLC
Category: prescription | Type: HUMAN PRESCRIPTION DRUG LABEL
Date: 20100317

ACTIVE INGREDIENTS: Oxygen 1000 mL/1 L

PACKAGE LABEL

CARTON